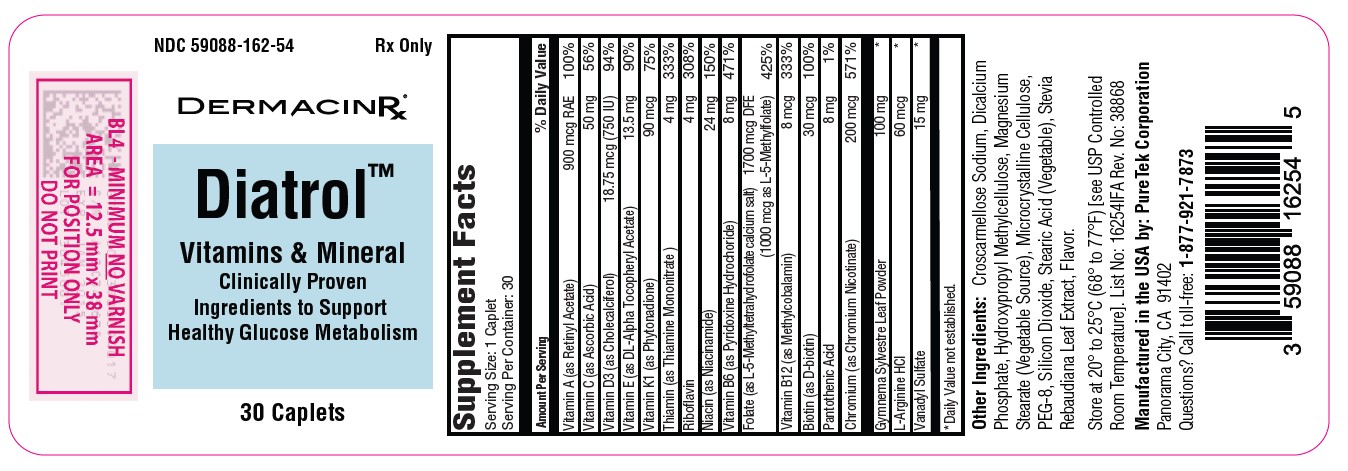 DRUG LABEL: Diatrol
NDC: 59088-162 | Form: CAPSULE
Manufacturer: PureTek Corporation
Category: prescription | Type: HUMAN PRESCRIPTION DRUG LABEL
Date: 20240401

ACTIVE INGREDIENTS: BIOTIN 30 ug/1 1; VANADYL SULFATE 15 mg/1 1; CHROMIUM NICOTINATE 200 ug/1 1; GYMNEMA SYLVESTRE LEAF 100 mg/1 1; ARGININE HYDROCHLORIDE 60 ug/1 1; .ALPHA.-TOCOPHEROL ACETATE, DL- 13.5 mg/1 1; PHYTONADIONE 90 ug/1 1; VITAMIN A 900 ug/1 1; ASCORBIC ACID 50 mg/1 1; CHOLECALCIFEROL 18.75 ug/1 1; PYRIDOXINE HYDROCHLORIDE 8 mg/1 1; THIAMINE MONONITRATE 4 mg/1 1; RIBOFLAVIN 4 mg/1 1; NIACIN 24 mg/1 1; LEVOMEFOLATE CALCIUM 1000 ug/1 1; METHYLCOBALAMIN 8 ug/1 1; PANTOTHENIC ACID 8 mg/1 1
INACTIVE INGREDIENTS: SILICON DIOXIDE; HYPROMELLOSES; STEVIA REBAUDIUNA LEAF; POLYETHYLENE GLYCOL 400; CROSCARMELLOSE SODIUM; MAGNESIUM STEARATE; CELLULOSE, MICROCRYSTALLINE; STEARIC ACID; DIBASIC CALCIUM PHOSPHATE DIHYDRATE

Diatrol

Each Caplet Contains:

Vitamin A (as Retinyl Acetate).................................... 900 mcg RAE
Vitamin C (as Ascorbic Acid)................................................. 50 mg
Vitamin D3 (as Cholecalciferol)....................................... 18.75 mcg
Vitamin E (as DL-Alpha Tocopheryl Acetate)...................... 13.5 mg
Vitamin K1 (as Phytonadione)............................................. 90 mcg
Thiamin (as Thiamine Mononitrate)......................................... 4 mg
Riboflavin ................................................................................. 4 mg
Niacin (as Niacinamide)......................................................... 24 mg
Vitamin B6 (as Pyridoxine Hydrochloride)............................... 8 mg
Folate (as L-5-Methyltetrahydrofolate calcium salt)…1700 mcg DFE
(1000 mcg as L-5-Methylfolate)
Vitamin B12 (as Methylcobalamin)........................................ 8 mcg
Biotin (as D-biotin)............................................................... 30 mcg
Pantothenic Acid ...................................................................... 8 mg
Chromium (as Chromium Nicotinate)............................... 200 mcg
Gymnema Sylvestre Leaf Powder........................................ 100 mg
L-Arginine HCl...................................................................... 60 mcg
Vanadyl Sulfate....................................................................... 15 mg

Other Ingredients:

Croscarmellose Sodium, Dicalcium Phosphate, Hydroxypropyl Methylcellulose, Magnesium Stearate (Vegetable Source), Microcrystalline Cellulose, PEG-8, Silicon Dioxide, Stearic Acid (Vegetable), Stevia Rebaudiana Leaf Extract, Flavor.

INDICATIONS AND USAGE

Diatrol™ is indicated to provide significant amounts of essential vitamins and mineral. This comprehensive nutrient profile helps prevent nutritional deficiencies of these vitamins and minerals, ensuring that the specific dietary needs are met to support overall health, energy, and vitality. The product is specially formulated to target common vitamin and mineral gaps, thus promoting optimal health, immune function, bone strength, and metabolic balance. It is intended to be used under the guidance of a licensed healthcare practitioner to ensure that any potential for nutritional deficiency is addressed in a manner that supports the individual's overall health and wellbeing.

Contraindications:

This product is contraindicated in patients with known hypersensitivity to any of its ingredients.

WARNING

In case of accidental overdose, seek professional assistance or contact a Poison Control Center immediately.

PRECAUTIONS

Folate doses above 0.1 mg daily may obscure pernicious anemia, in that hematologic remission can occur while neurological manifestations remain progressive. There is a potential danger in administering folate to patients with undiagnosed anemia, since folate may obscure the diagnosis of pernicious anemia by alleviating the hematologic manifestations of the disease while allowing the neurologic complications to progress. This may result in severe nervous system damage before the correct diagnosis is made. Adequate doses of vitamin B12 may prevent, halt, or improve the neurologic changes caused by pernicious anemia.

The patient’s medical conditions and consumption of other drugs, herbs, and/or supplements should be considered.

For use on the order of a licensed healthcare practitioner. Call your doctor about side effects. To report side effects, call PureTek Corporation at 1-877-921-7873 or FDA at 1-800-FDA-1088 or www.fda.gov/medwatch.

Adverse Reactions:

Folate: Allergic sensitizations has been reported following both oral and parenteral administration of folate. Adverse reactions have been reported with specific vitamins and minerals but generally at levels substantially higher than those contained herein. However, allergic and idiosyncratic reactions are possible at lower levels.

DOSAGE AND ADMINISTRATION

Take one (1) caplet daily or as directed by a licensed healthcare practitioner.

HOW SUPPLIED

Diatrol™ caplets are light green with brown speckles and dispensed in a child-resistant bottle containing 30 caplets (NDC 59088-162-54). All prescription substitutions using this product shall be pursuant to state statutes as applicable. This is not an Orange Book product.

STORAGE

Do not use if bottle seal is broken.
KEEP THIS AND ALL MEDICATIONS OUT OF THE REACH OF CHILDREN.
Store at 20° to 25°C (68° to 77°F) [see USP Controlled Room Temperature].

Protect from light and moisture and avoid excessive heat.

Diatrol™

Manufactured in the USA by:
PureTek Corporation
Panorama City, CA 91402
Questions? Call toll-free:
1-877-921-7873